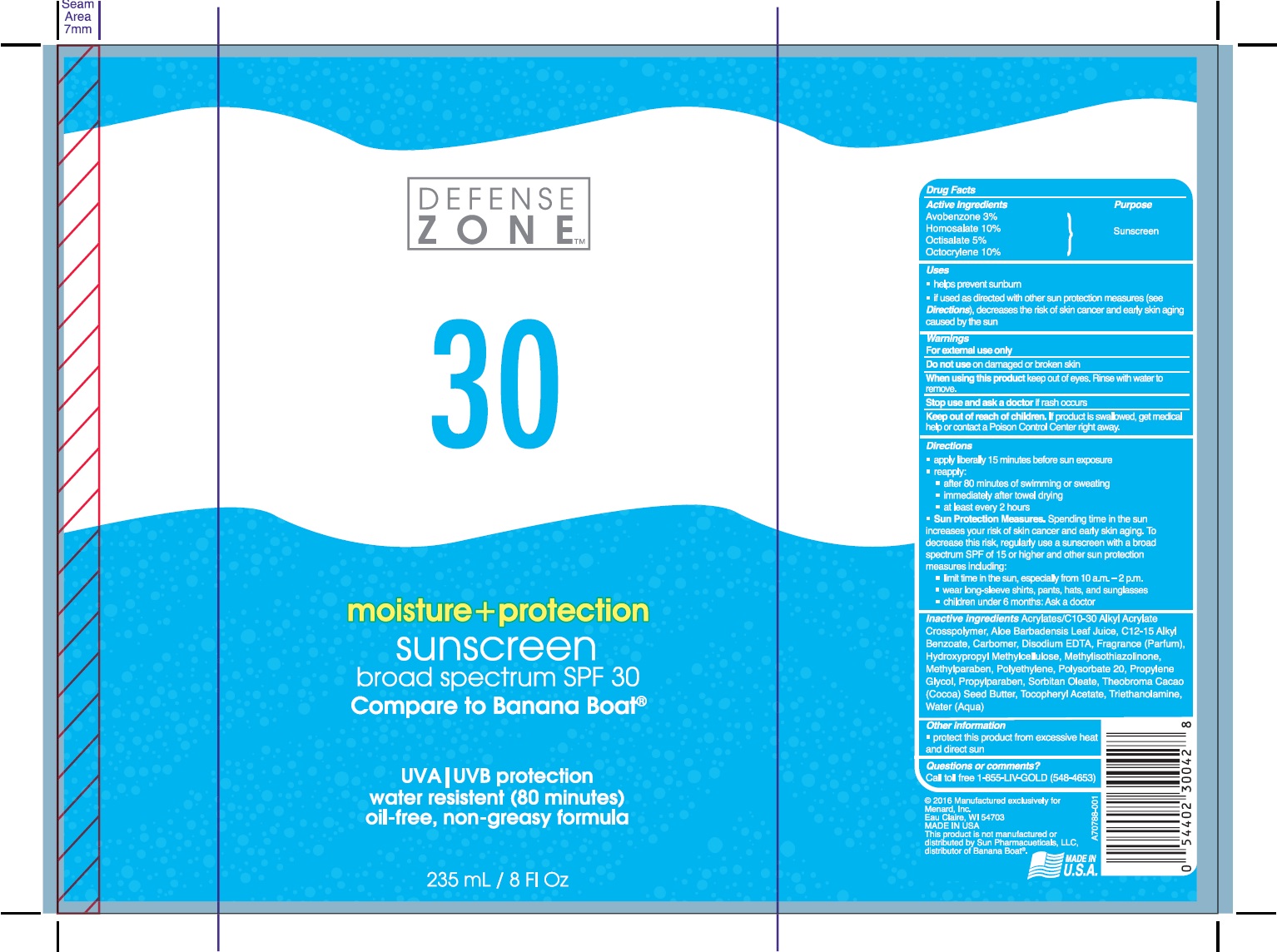 DRUG LABEL: Defense Zone
NDC: 58443-0232 | Form: LOTION
Manufacturer: Prime Enterprises Inc.
Category: otc | Type: HUMAN OTC DRUG LABEL
Date: 20200117

ACTIVE INGREDIENTS: AVOBENZONE 29.7 mg/1 mL; HOMOSALATE 98.9 mg/1 mL; OCTISALATE 49.5 mg/1 mL; OCTOCRYLENE 98.9 mg/1 mL
INACTIVE INGREDIENTS: ALKYL (C12-15) BENZOATE; WATER; SORBITAN MONOOLEATE; HIGH DENSITY POLYETHYLENE; POLYSORBATE 20; COCOA BUTTER; EDETATE DISODIUM; TROLAMINE; METHYLISOTHIAZOLINONE; METHYLPARABEN; PROPYLPARABEN; HYPROMELLOSES; PROPYLENE GLYCOL; ALOE VERA LEAF; CARBOMER 940; CARBOMER COPOLYMER TYPE A (ALLYL PENTAERYTHRITOL CROSSLINKED); ALPHA-TOCOPHEROL ACETATE

Defense Zone Broad Spectrum SPF 30 Sunscreen

Active Ingredients

Avobenzone 3%

Homosalate 10%

Octisalate 5%

Octocrylene 10%

Purpose

Sunscreen

Uses

- helps prevent sunburn
- if used as directed with other sun protection measures (see Directions), decreases the risk of skin cancer and early skin aging caused by the sun.

Warnings

For external use only.

Do not use on damaged or broken skin

When using this product keep out of eyes. Rinse with water to remove.

Stop use and ask a doctor if rash occurs

Keep out of reach of children. If product is swallowed, get medical help or contact a Poison Control Center right away.

Directions

- apply liberally 15 minutes before sun exposure
- reapply:
- after 80 minutes of swimming or sweating
- immediately after towel drying
- at least every 2 hours
- Sun Protection Measures. Spending time in the sun increases your risk of skin cancer and early skin aging. To decrease this risk, regularly use a sunscreen with a broad spectrum SPF of 15 or higher and other sun protection measures including:
- limit time in the sun, especially from 10 a.m. – 2 p.m.
- wear long-sleeve shirts, pants, hats, and sunglasses
- children under 6 months: Ask a doctor

INACTIVE INGREDIENT

Acrylates/C10-30 Alkyl Acrylate Crosspolymer, Aloe Barbadensis Leaf Juice, C12-15 Alkyl Benzoate, Carbomer, Disodium EDTA, Fragrance (Parfum), Hydroxypropyl Methylcellulose, Methylisothiazolinone, Methylparaben, Polyethylene, Polysorbate 20, Propylene Glycol, Propylparaben, Sorbitan Oleate, Theobroma Cacao (Cocoa) Seed Butter, Tocopheryl Acetate, Triethanolamine, Water (Aqua)

Other Information

- protect this product from excessive heat and direct sun

Questions or Comments?

Call toll free 1-855-LIV-GOLD (548-4653)